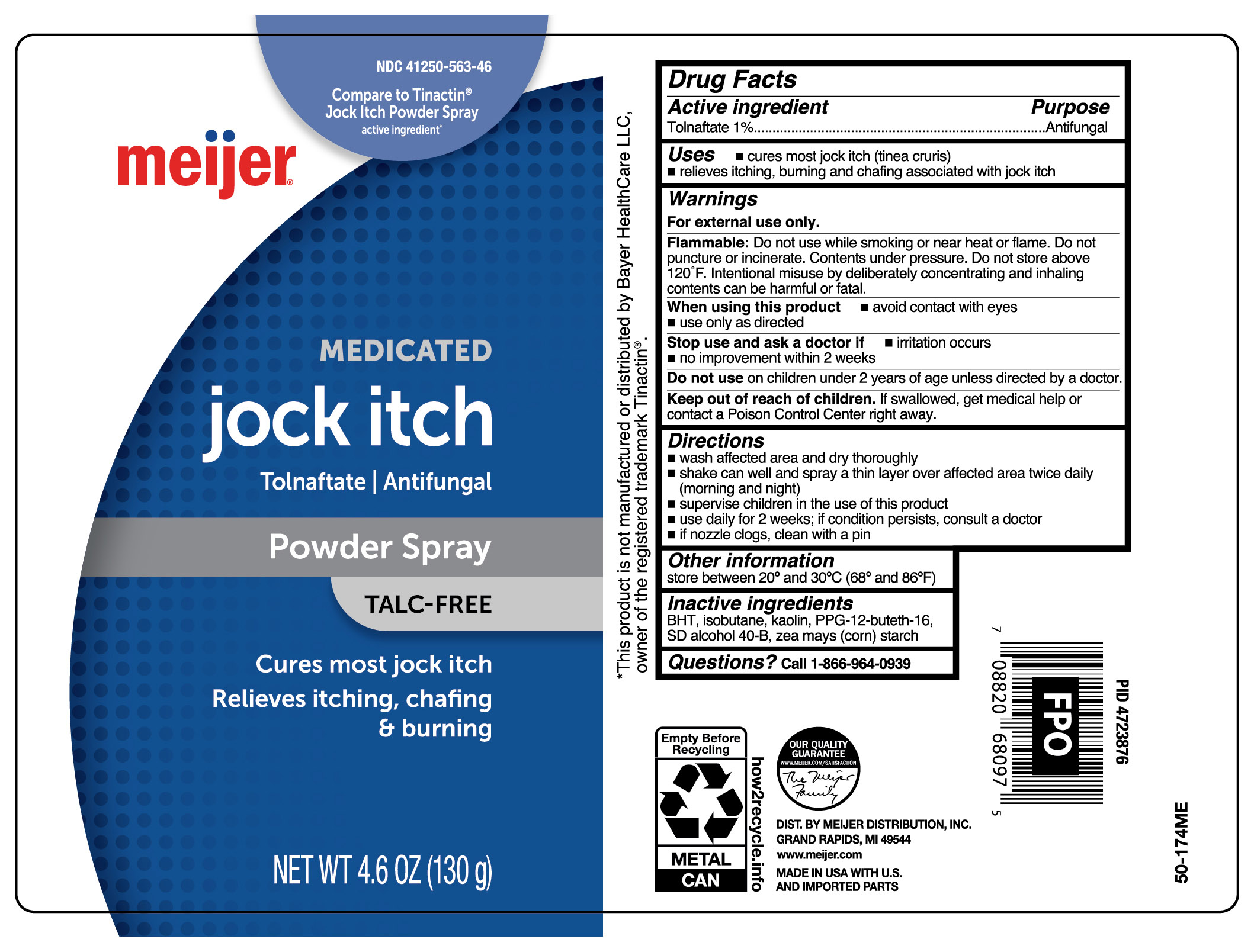 DRUG LABEL: Tolnaftate
NDC: 41250-563 | Form: AEROSOL, SPRAY
Manufacturer: Meijer Distribution Inc
Category: otc | Type: HUMAN OTC DRUG LABEL
Date: 20241014

ACTIVE INGREDIENTS: TOLNAFTATE 1.3 g/130 g
INACTIVE INGREDIENTS: ALCOHOL; KAOLIN; ZEA MAYS SUBSP. MAYS WHOLE; BUTYLATED HYDROXYTOLUENE; PPG-12-BUTETH-16; ISOBUTANE

Meijer Antifungal Tolnaftate Jock Itch Powder Spray - Talc Free

Active ingredient

Tolnaftate 1%

Purpose

Antifungal

Uses

- cures most jock itch (tinea cruris)
- relieves itching, burning a d chafing associated with jock itch

Warnings

For external use only.

Flammable:

Do not use while smoking or near heat or flame. Do not puncture or incinerate. Contents under pressure. Do not store above 120°F. Intentional misuse by deliberately concentrating and inhaling contents can be harmful or fatal.

When using this product

- avoid contact with eyes
- use only as directed

Stop use and ask a doctor if

- irritation occurs
- no improvement within 2 weeks

Do not use

on children under 2 years of age unless directed by a doctor.

Keep out of reach of children.

If swallowed, get medical help or contact a Poison Control Center right away.

Directions

- wash affected area and dry thoroughly
- shake can well and spray a thin layer over affected area twice daily (morning and night)
- supervise children in the use of this product
- use daily for 2 weeks; if condition persists, consult a doctor
- if nozzle clogs, clean with a pin

Other information

store between 20º and 30ºC (68º and 86ºF)

Inactive ingredients

BHT, isobutane, kaolin, PPG-12-buteth-16, SD alcohol 40-B, zea mays (corn) starch

Questions?

Call 1-866-964-0939

Principal Display Panel

meijer

MEDICATED

jock itch

Tolnaftate | Antifungal

Powder Spray

TALC-FREE

Cures most jock itch

Relieves itching, chafing & burning

NET WT 4.6 OZ (130 g)